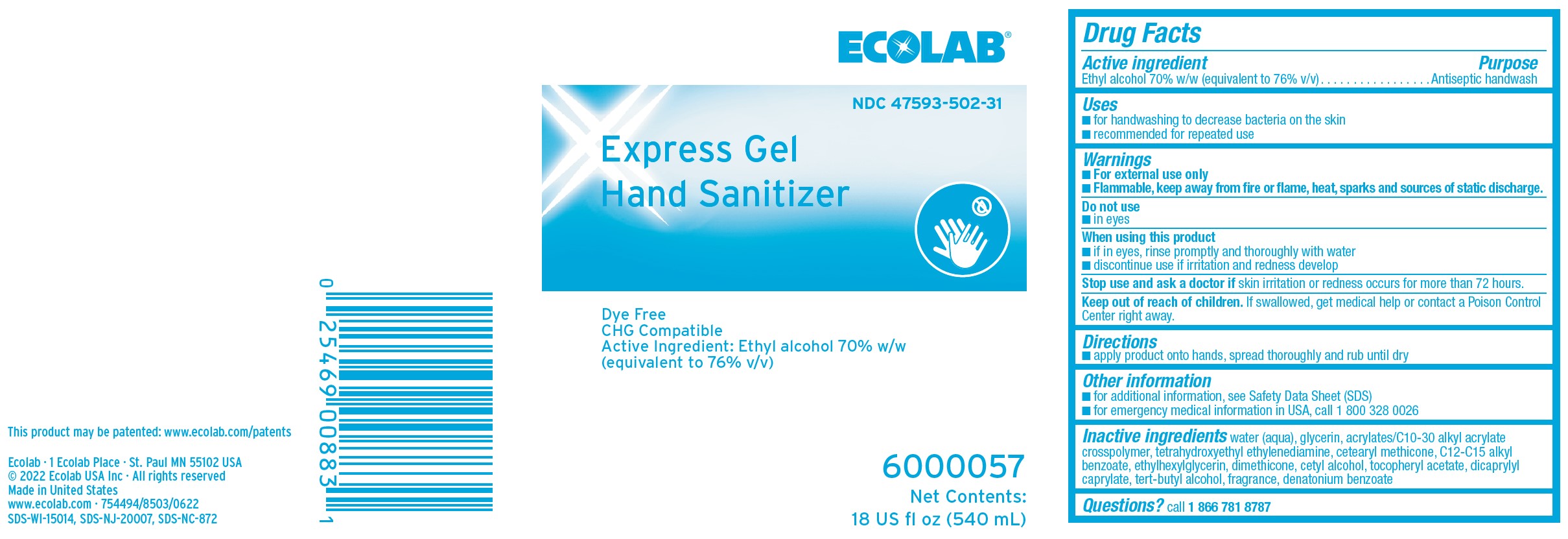 DRUG LABEL: Ecolab
NDC: 47593-502 | Form: SOLUTION
Manufacturer: Ecolab Inc.
Category: otc | Type: HUMAN OTC DRUG LABEL
Date: 20250920

ACTIVE INGREDIENTS: ALCOHOL 598.5 mg/1 mL
INACTIVE INGREDIENTS: WATER; GLYCERIN; CARBOMER INTERPOLYMER TYPE A (ALLYL SUCROSE CROSSLINKED); ETHYLENEDIAMINE TETRAETHANOL; CETEARYL METHICONE (15000 MW); ALKYL (C12-15) BENZOATE; ETHYLHEXYLGLYCERIN; DIMETHICONE; CETYL ALCOHOL; .ALPHA.-TOCOPHEROL ACETATE; DICAPRYLYL CARBONATE; TERT-BUTYL ALCOHOL; DENATONIUM BENZOATE

Drug Facts

Active ingredient

Ethyl alcohol 70% w/w (equivalent to 76% v/v)

Purpose

Antiseptic handwash

Uses

- For handwashing to decrease bacteria on the skin
- Recommended for repeated use

Warnings

- For external use only
- Flammable, keep away from fire or flame, sparks and sources of static discharge

Do not use

- In eyes

When using this product

- If in eyes, rinse promptly and thoroughly with water
- Discontinue use if irritation and redness develop

ASK DOCTOR

Stop and ask a doctor if skin irritation or redness occurs for more than 72 hours.

Keep out of reach of children. If swallowed, get medical help or contact a Poison Control Center right away.

Directions

- Apply product onto hands, spread thoroughly and rub until dry

Other information

- for additional information, see Safety Data Sheet (SDS)
- for emergency medical information in USA, call 1 800 328 0026

INACTIVE INGREDIENT

Inactive ingredients water (aqua), glycerin, acrylates/C10-30 alkyl acrylate crosspolymer, tetrahydroxyethyl ethylenediamine, cetearyl methicone, C12-C15 alkyl benzoate, ethylhexylglycerin, dimethicone, cetyl alcohol, tocopheryl acetate, dicaprylyl caprylate, tert-butyl alcohol, fragrance, dentaonium benzoate

Questions? call 1 866 781 8787

Principal Display Panel and Representative Label

ECOLAB®

NDC 47593-502-31

Express Gel

Hand Sanitizer

Dye Free

CHG Compatible

Active Ingredient: Ethyl alcohol 70% w/w

(equivalent to 76% v/v)

6000057

Net Contents:

18 US fl oz (540 mL)

Ecolab · 1 Ecolab Place · St. Paul MN 55102 USA

© 2022 Ecolab USA Inc · All rights reserved

Made in United States

www.ecolab.com · 754494/8503/0622

SDS-WI-15014, SDS-NJ-20007, SDS-NC-872